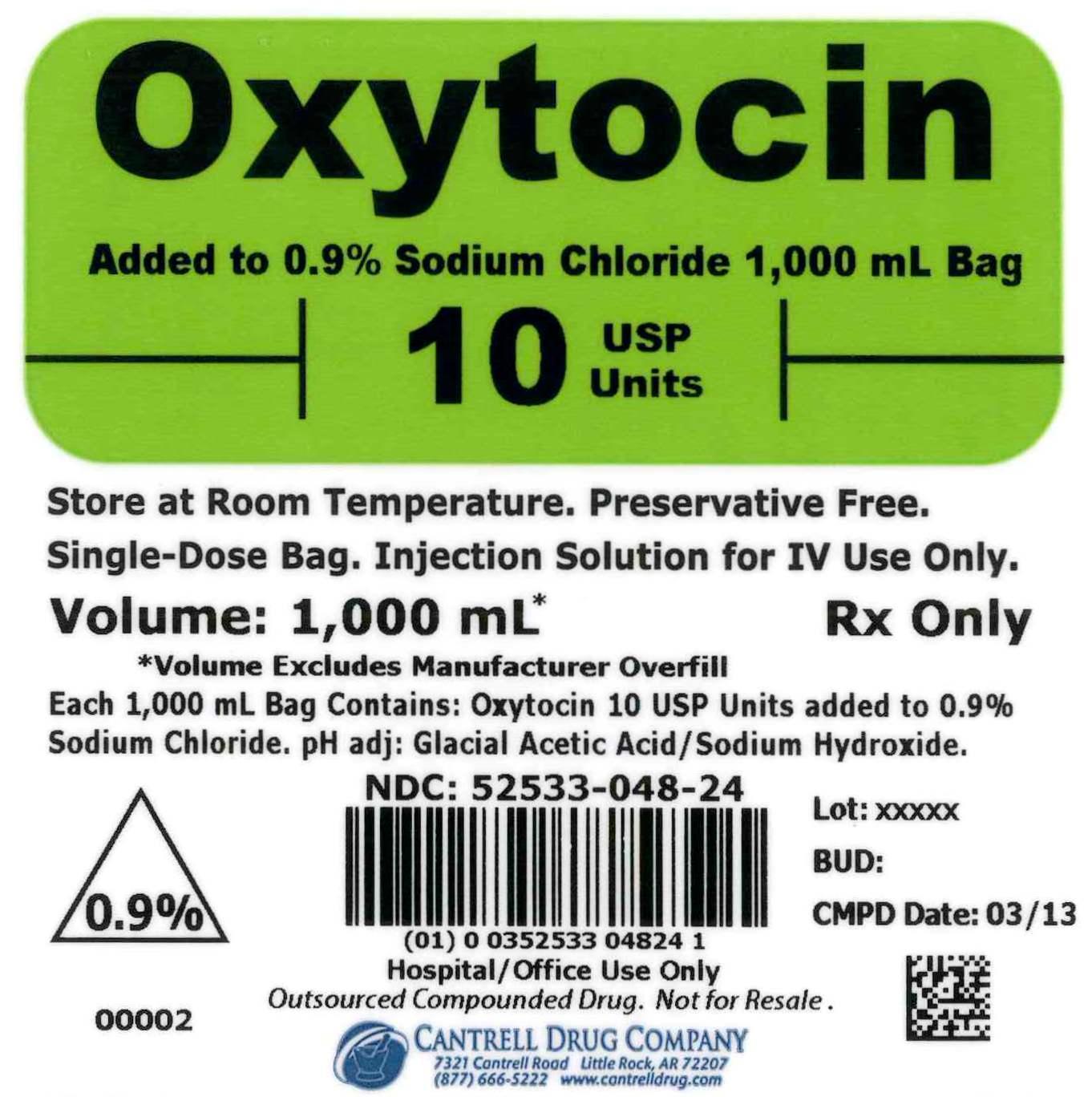 DRUG LABEL: Oxytocin
NDC: 52533-048 | Form: INJECTION, SOLUTION
Manufacturer: Cantrell Drug Company
Category: prescription | Type: HUMAN PRESCRIPTION DRUG LABEL
Date: 20141211

ACTIVE INGREDIENTS: OXYTOCIN 10 [USP'U]/1000 mL
INACTIVE INGREDIENTS: SODIUM CHLORIDE 9 g/1000 mL; WATER

Oxytocin 10 USP Units Added to 0.9% Sodium Chloride 1,000 mL Bag